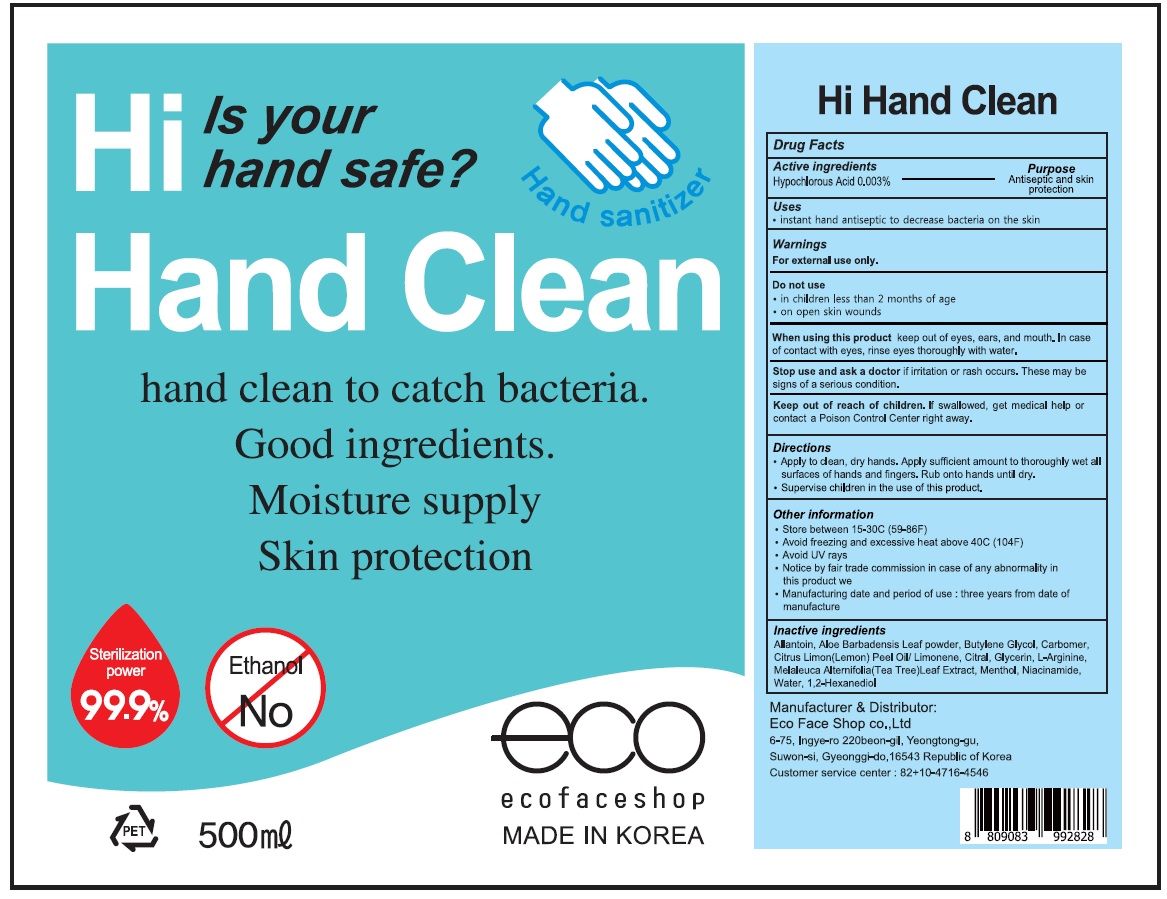 DRUG LABEL: Hi Hand Clean
NDC: 71672-030 | Form: LIQUID
Manufacturer: Eco Face Shop
Category: otc | Type: HUMAN OTC DRUG LABEL
Date: 20200907

ACTIVE INGREDIENTS: HYPOCHLOROUS ACID 0.015 g/500 mL
INACTIVE INGREDIENTS: Allantoin; ALOE VERA LEAF; Butylene Glycol; CARBOMER HOMOPOLYMER, UNSPECIFIED TYPE; Glycerin; Menthol; Niacinamide; Water; 1,2-Hexanediol

ACTIVE INGREDIENT

Hypochlorous Acid 0.003%

INACTIVE INGREDIENTS

Allantoin, Aloe Barbadensis Leaf powder, Butylene Glycol, Carbomer, Citrus Limon(Lemon) Peel Oil/ Limonene, Citral, Glycerin, L-Arginine, Melaleuca Alternifolia(Tea Tree)Leaf Extract, Menthol, Niacinamide, Water, 1,2-Hexanediol

PURPOSE

Antiseptic and skin protection

WARNINGS

For external use only.
--------------------------------------------------------------------------------------------------------
Do not use

• in childre n less than 2 months of age
• on open skin wounds
--------------------------------------------------------------------------------------------------------
When using this product keep out of eyes, ears, and mouth. In case of contact with eyes, rinse eyes thoroughly with water.
--------------------------------------------------------------------------------------------------------
Stop use and ask a doctor if irritation or rash occurs. These may be signs of a serious condition.

Keep out of reach of children. If swallowed, get medical help or contact a Poison Control Center right away.

Uses

• instant hand antiseptic to decrease bacteria on the skin

Directions

• Apply to clean, dry hands. Apply sufficient amount to thoroughly wet all surfaces of hands and fingers. Rub onto hands until dry.
• Supervise children in the use of this product.

Other information

• Store between 15-30C (59-86F)
• Avoid freezing and excessive heat above 40C (104F)
• Avoid UV rays
• Notice by fair trade commission in case of any abnormality in this product we •Manufacturing date and period of use : three years from date of manufacture